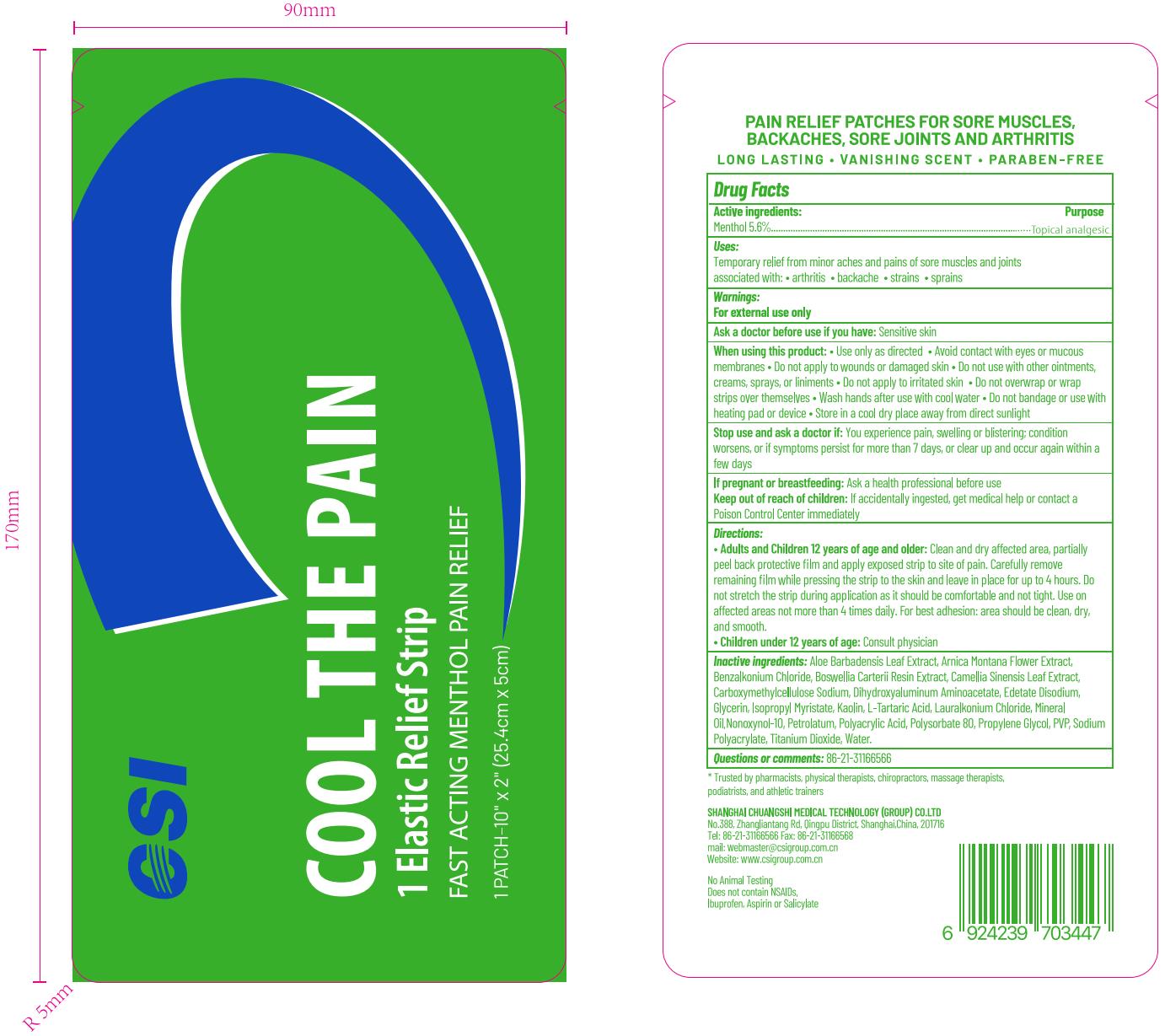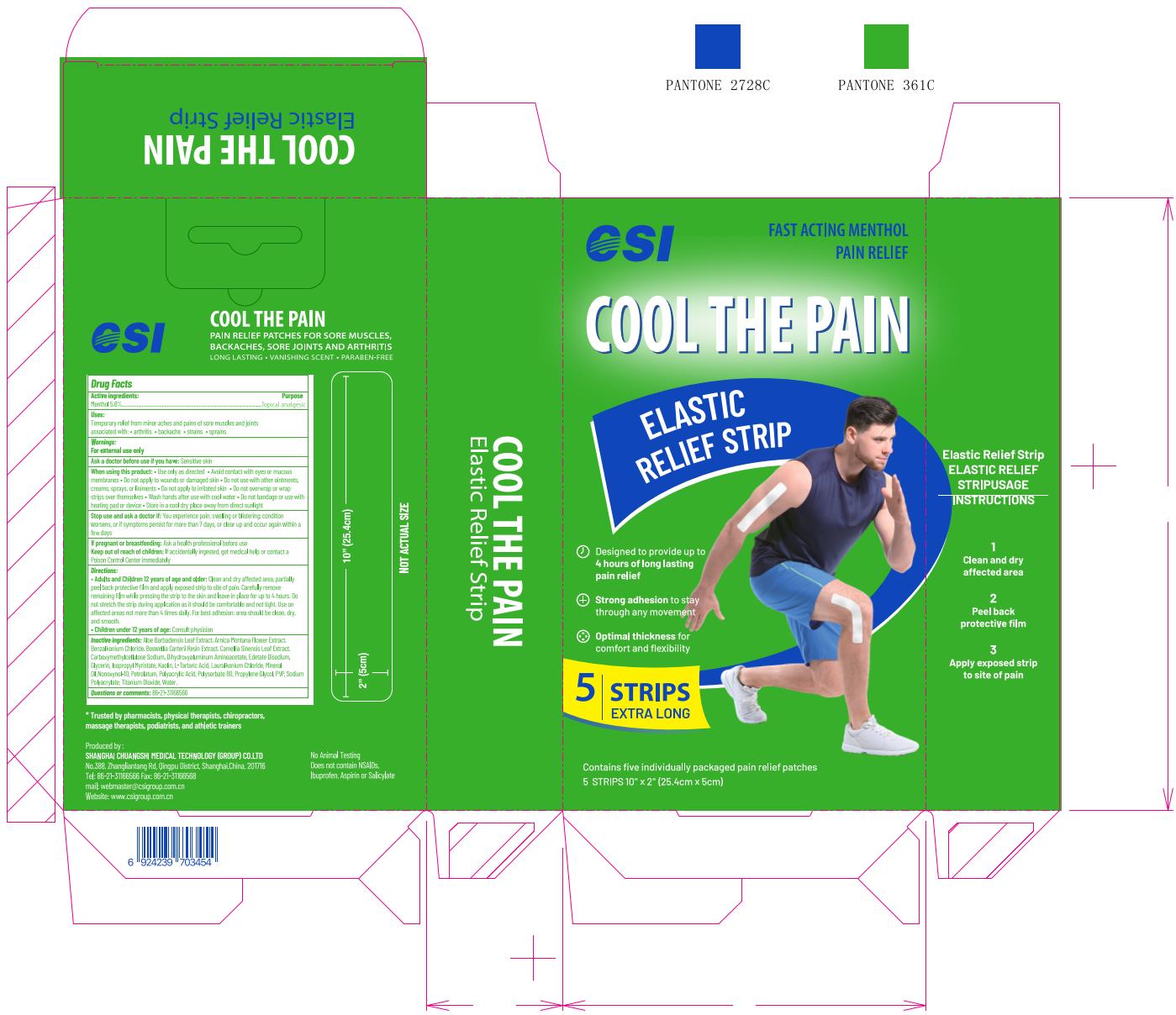 DRUG LABEL: Elastic Relief Strip
NDC: 73557-130 | Form: PATCH
Manufacturer: Shanghai Chuangshi Medical Technology (Group) Co., Ltd.
Category: otc | Type: HUMAN OTC DRUG LABEL
Date: 20240429

ACTIVE INGREDIENTS: MENTHOL 0.056 g/1 g
INACTIVE INGREDIENTS: POLYSORBATE 80 0.018 g/1 g; GLYCERIN 0.24 g/1 g; POVIDONE K90 0.012 g/1 g; GREEN TEA LEAF 0.0001 g/1 g; ALOE VERA LEAF 0.0001 g/1 g; EDETATE DISODIUM 0.001 g/1 g; ARNICA MONTANA FLOWER 0.0001 g/1 g; FRANKINCENSE 0.0001 g/1 g; KAOLIN 0.001 g/1 g; TARTARIC ACID 0.001 g/1 g; WATER 0.30808 g/1 g; DIHYDROXYALUMINUM AMINOACETATE ANHYDROUS 0.0015 g/1 g; PROPYLENE GLYCOL 0.07 g/1 g; POLYACRYLIC ACID (250000 MW) 0.2 g/1 g; CARBOXYMETHYLCELLULOSE SODIUM 0.001 g/1 g; SODIUM POLYACRYLATE (2500000 MW) 0.05 g/1 g; TITANIUM DIOXIDE 0.001 g/1 g; MINERAL OIL 0.03 g/1 g; PETROLATUM 0.002 g/1 g; BENZALKONIUM CHLORIDE 0.001 g/1 g; LAURALKONIUM CHLORIDE 0.001 g/1 g; NONOXYNOL-10 0.00002 g/1 g; ISOPROPYL MYRISTATE 0.005 g/1 g

CSI Elastic Relief Strip, 5 Strips

Active ingredient

Menthol 5.6% ...... Purpose: Topical Analgesic

Purpose

Topical Analgesic

Uses

Temporary relief from minor aches and pains of sore muscles and joints associated with:

- arthrits
- backache
- strains
- sprains

Warnings

- For external use only
- Use only as directed
- Avoid contact with eyes or mucous membranes
- Do not apply to wounds or damaged skin
- Do not use with other ointments, creams, sprays, or liniments
- Do not apply to irritated skin
- Do not overwrap or wrap strips over themselves
- Do not bandage or use with heating pad or device

Ask doctor

Stop use and ask a doctor if: You experience pain, swelling or blistering; condition worsens, or if symptoms persist for more than 7 days, or clear up and occur again within a few days

When using

- Use only as directed
- Avoid contact with eyes or mucous membranes
- Do not apply to wounds or damaged skin
- Do not use with other ointments, creams, sprays, or liniments
- Do not apply to irritated skin
- Do not overwrap or wrap strips over themselves
- Wash hands after use with cool water
- Do not bandage or use with heating pad or device

Do not use

- Do not apply to wounds or damaged skin
- Do not use with other ointments, creams, sprays, or liniments
- Do not apply to irritated skin
- Do not overwrap or wrap strips over themselves
- Do not bandage or use with heating pad or device

Stop use

Stop use and ask a doctor if: You experience pain, swelling or blistering; condition worsens, or if symptoms persist for more than 7 days, or clear up and occur again within a few days

Pregnancy or breast feeding

If pregnant or breastfeeding: Ask a health professional before use

Keep out of reach of children: If accidentally ingested, get medical help or contact a Poison Control Center immediately.

Directions

- Adult and Children 12 years of age and older: Clean and dry affected area, partially peel back protective film and apply exposed strip to site of pain. Carefully remove remaining film while pressing the strip to the skin and leave in place for up to 4 hours. Do not strech the strip during application as it should be comfortable and not tight. Use on affected areas not more than 4 times daily. For best adhesion: area should be clean, dry, and smooth.
- Children under 12 years of age: Consult physician

Dosage forms & strengths

This is a strip, patch dosage form.

The active ingredient strength is 5.6%.

Questions

Questions or comments: 86-21-31166566

Other information

- Store in a cool dry place away from direct sunlight